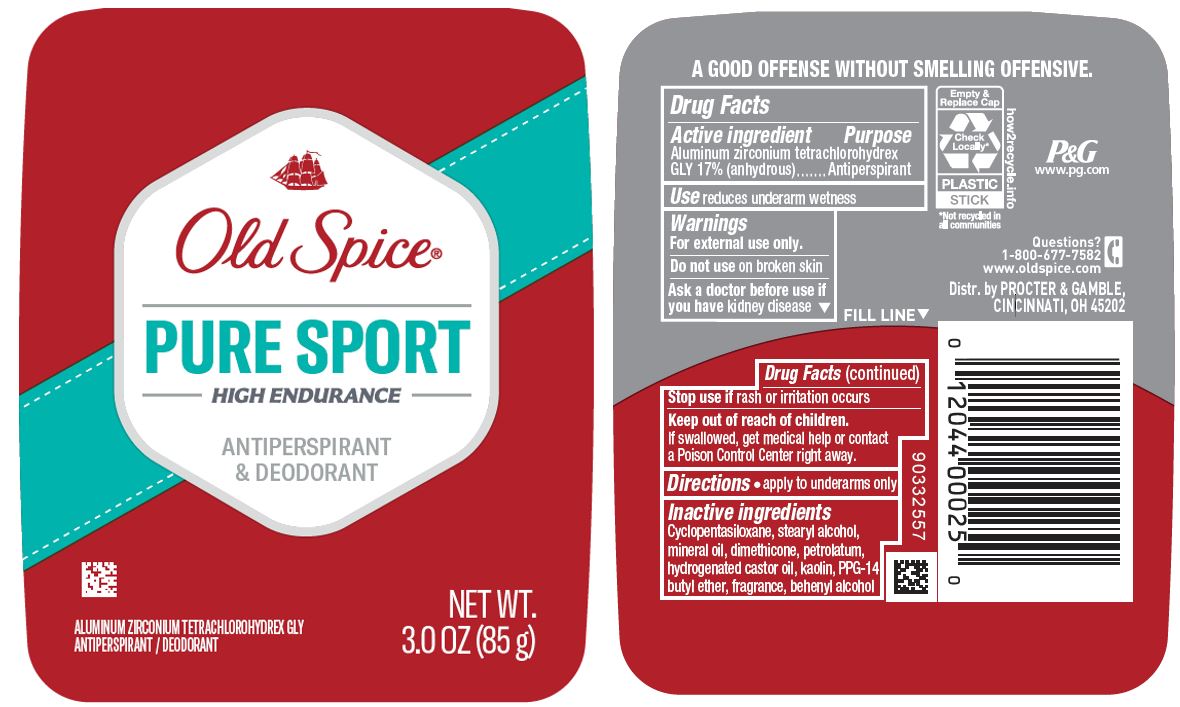 DRUG LABEL: Old Spice High Endurance Pure Sport
NDC: 69423-542 | Form: STICK
Manufacturer: The Procter & Gamble Manufacturing Company
Category: otc | Type: HUMAN OTC DRUG LABEL
Date: 20251231

ACTIVE INGREDIENTS: ALUMINUM ZIRCONIUM TETRACHLOROHYDREX GLY 17 g/100 g
INACTIVE INGREDIENTS: DIMETHICONE; CYCLOMETHICONE 5; STEARYL ALCOHOL; MINERAL OIL; KAOLIN; HYDROGENATED CASTOR OIL; PPG-14 BUTYL ETHER; DOCOSANOL; PETROLATUM

Old Spice® High Endurance Pure Sport Invisible Solid

Drug Facts

Active ingredient

Aluminum zirconium tetrachlorohydrex Gly 17% (anhydrous)

Purpose

Antiperspirant

Use

reduces underarm wetness

Warnings

For external use only.

Do not use on broken skin

Ask a doctor before use if you have kidney disease

Stop use if rash or irritation occurs

Keep out of reach of children.
If swallowed, get medical help or contact a Poison Control Center right away.

Directions

- apply to underarms only

Inactive ingredients

Cyclopentasiloxane, stearyl alcohol, mineral oil, dimethicone, petrolatum, hydrogenated castor oil, kaolin, PPG-14 butyl ether, fragrance, behenyl alcohol

Questions?

1-800-677-7582

Dist. by PROCTER & GAMBLE,
CINCINNATI, OH 45202.

PRINCIPAL DISPLAY PANEL - 85 g Cylinder Label

Old Spice ®

Pure Sport

High Endurance

ANTIPERSPIRANT

& DEODORANT

ALUMINUM ZIRCONIUM TETRACHLOROHYDREX GLY

ANTIPERSPIRANT/DEODORANT

NET WT. 3.0 OZ (85 g)